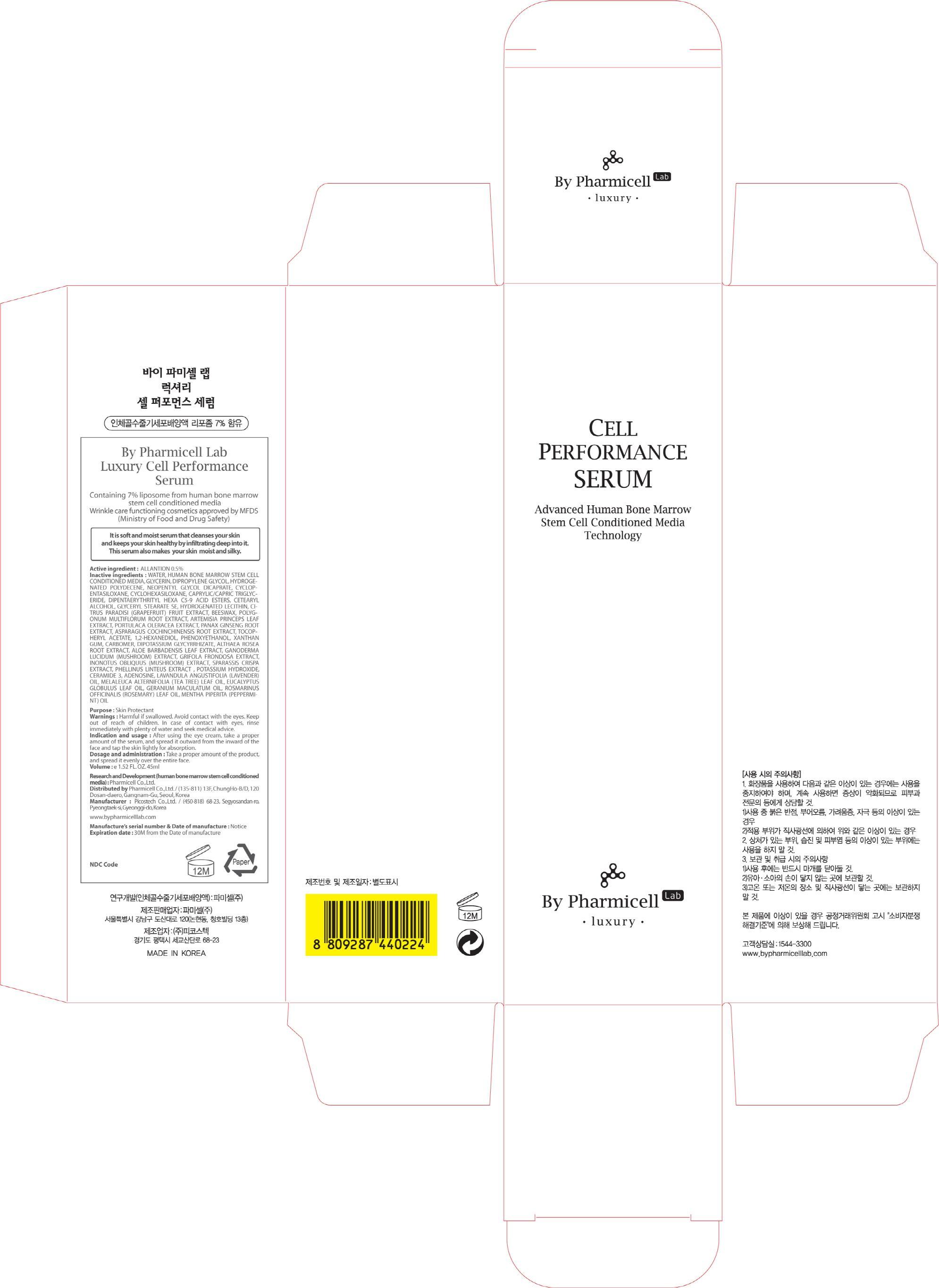 DRUG LABEL: Luxury Cell Performance Serum
NDC: 60949-140 | Form: CREAM
Manufacturer: Pharmicell Co., Ltd.
Category: otc | Type: HUMAN OTC DRUG LABEL
Date: 20140922

ACTIVE INGREDIENTS: ALLANTOIN 0.22 mg/45 mL
INACTIVE INGREDIENTS: WATER; GLYCERIN

ACTIVE INGREDIENT

Active ingredient : ALLANTOIN 0.5%

INACTIVE INGREDIENT

Inactive ingredients : WATER, HUMAN BONE MARROW STEM CELL CONDITIONED MEDIA, GLYCERIN, DIPROPYLENE GLYCOL, HYDROGENATED POLYDECENE, NEOPENTYL GLYCOL DICAPRATE, CYCLOPENTASILOXANE, CYCLOHEXASILOXANE, CAPRYLIC/CAPRIC TRIGLYCERIDE, DIPENTAERYTHRITYL HEXA C5-9 ACID ESTERS, CETEARYL ALCOHOL, GLYCERYL STEARATE SE, HYDROGENATED LECITHIN, CITRUS PARADISI (GRAPEFRUIT) FRUIT EXTRACT, BEESWAX, POLYGONUM MULTIFLORUM ROOT EXTRACT, ARTEMISIA PRINCEPS LEAF EXTRACT, PORTULACA OLERACEA EXTRACT, PANAX GINSENG ROOT EXTRACT, ASPARAGUS COCHINCHINENSIS ROOT EXTRACT, TOCOPHERYL ACETATE, 1,2-HEXANEDIOL, PHENOXYETHANOL, XANTHAN GUM, CARBOMER, DIPOTASSIUM GLYCYRRHIZATE, ALTHAEA ROSEA ROOT EXTRACT, ALOE BARBADENSIS LEAF EXTRACT, GANODERMA LUCIDUM (MUSHROOM) EXTRACT, GRIFOLA FRONDOSA EXTRACT, INONOTUS OBLIQUUS (MUSHROOM) EXTRACT, SPARASSIS CRISPA EXTRACT, PHELLINUS LINTEUS EXTRACT , POTASSIUM HYDROXIDE, CERAMIDE 3, ADENOSINE, LAVANDULA ANGUSTIFOLIA (LAVENDER) OIL, MELALEUCA ALTERNIFOLIA (TEA TREE) LEAF OIL, EUCALYPTUS GLOBULUS LEAF OIL, GERANIUM MACULATUM OIL, ROSMARINUS OFFICINALIS (ROSEMARY) LEAF OIL, MENTHA PIPERITA (PEPPERMINT) OIL

PURPOSE

Purpose : Skin Protectant

WARNINGS

Warnings : Harmful if swallowed. Avoid contact with the eyes. Keep out of reach of children. In case of contact with eyes, rinse immediately with plenty of water and seek medical advice.

KEEP OUT OF REACH OF CHILDREN

INDICATIONS & USAGE

Indication and usage : After using the eye cream, take a proper amount of the serum, and spread it outward from the inward of the face and tap the skin lightly for absorption.

DOSAGE & ADMINISTRATION

Dosage and administration : Take a proper amount of the product, and spread it evenly over the entire face.